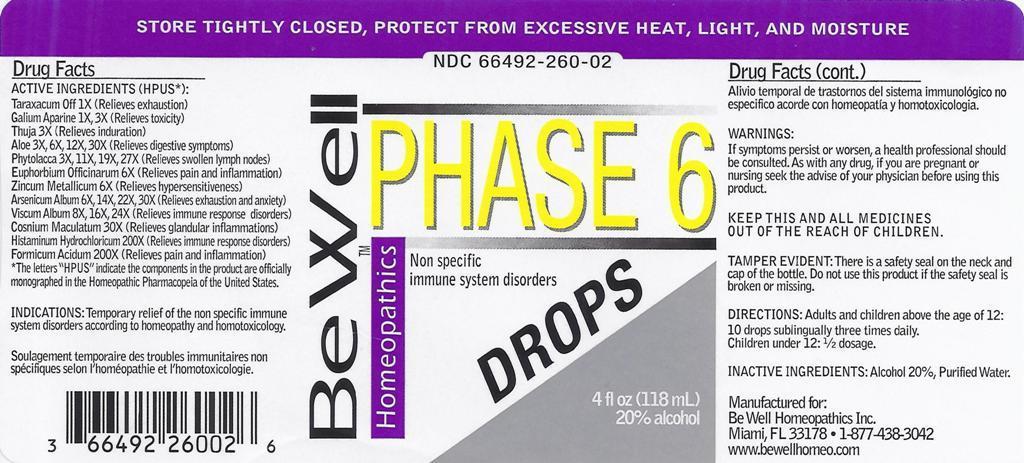 DRUG LABEL: Phase 6 Drops
NDC: 66492-260 | Form: LIQUID
Manufacturer: Be Well Medical dba Richard Clement Nutrition y Be Well Homeopathics
Category: homeopathic | Type: HUMAN OTC DRUG LABEL
Date: 20211229

ACTIVE INGREDIENTS: TARAXACUM OFFICINALE 1 [hp_X]/1 mL; GALIUM APARINE 1 [hp_X]/1 mL; THUJA OCCIDENTALIS LEAFY TWIG 3 [hp_X]/1 mL; ALOE 3 [hp_X]/1 mL; PHYTOLACCA AMERICANA ROOT 3 [hp_X]/1 mL; EUPHORBIA RESINIFERA RESIN 6 [hp_X]/1 mL; ZINC 6 [hp_X]/1 mL; ARSENIC TRIOXIDE 6 [hp_X]/1 mL; VISCUM ALBUM FRUITING TOP 8 [hp_X]/1 mL; CONIUM MACULATUM FLOWERING TOP 30 [hp_X]/1 mL; HISTAMINE DIHYDROCHLORIDE 200 [hp_X]/1 mL; FORMIC ACID 200 [hp_X]/1 mL
INACTIVE INGREDIENTS: WATER; ALCOHOL

PHASE 6 DROPS

ACTIVE INGREDIENTS (HPUS*):

Taraxacum Off 1X (Relieves exhaustion)

Galium Aparine 1X, 3X (Relieves toxicity)

Thuja 3X (Relieves induration)

Aloe 3X, 6X, 12X, 30X (Relieves digestive symptoms)

Phytolacca 3X, 11X, 19X, 27X (Relieves swollen lymph nodes)

Euphorbium Officinarum 6X (Relieves pain and inflammation)

Zincum Metallicum 6X (Relieves hypersensitiveness)

Arsenium Album 6X, 14X, 22X, 30X (Relieves exhaustion and anxiety)

Viscum Album 8X, 16X, 24X (Relieves immune response disorders)

Conium Maculatum 30X (Relieves glandular inflammations)

Histaminum Hydrochloricum 200X (Relieves immune response disorders)

Formicum Acidum 200X (Relieves pain and inflammation)

*The letters "HPUS" indicate the components in the product are officially monographed in the Homeopathic Pharmacopeia of the United States.

INDICATIONS AND USAGE

INDICATIONS: Temporary relief of the non specific immune system disorders according to homeopathy and homotoxicology.

Soulagement temporaire des troubles immunitaires non specifiques selon l'homeopathie et l'homotoxicologie. Alivio temporal de trastornos del sistema immunologico no especifico acorde con homeopatia y homotoxicologia.

WARNINGS:

If symptoms persist or worsen, a health professional should be consulted. As with any drug, if you are pregnant or nursing seek the advise of your physician before using this product.

KEEP THIS AND ALL MEDICINES OUT OF THE REACH OF CHILDREN.

OTHER SAFETY INFORMATION

TAMPER EVIDENT: There is a safety seal on the neck and cap of the bottle. Do not use this product if safety seal is broken or missing.

Store tightly closed, protect from excessive heat, light, and moisture.

DOSAGE AND ADMINISTRATION

DIRECTIONS: Adults and children above the age of 12: 10 drops sublingually three times daily.

Children under 12: 1/2 dosage.

INACTIVE INGREDIENTS: Alcohol 20%, Purified Water.

QUESTIONS

Manufactured for:

Be Well Homeopathics Inc.

Miami, FL 33178

1-877-438-3042

www.bewellhomeo.com

PACKAGE LABEL

NDC 66492-260-02

Be Well Homeopathics™

PHASE 6

DROPS

Non specific immune system disorders

4 fl oz (118 mL)

20% alcohol

PURPOSE

Non specific immune system disorders.